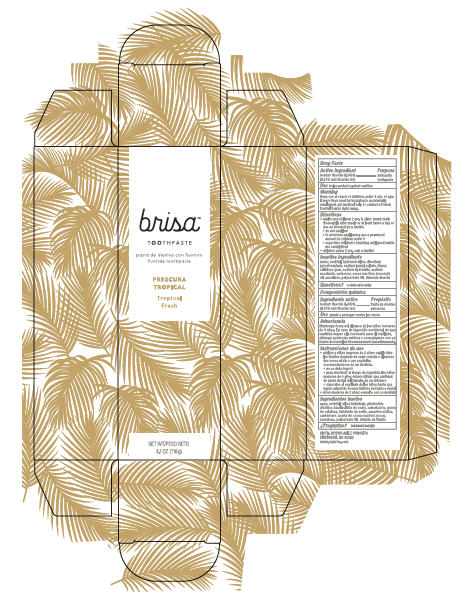 DRUG LABEL: Brisa
NDC: 73378-001 | Form: PASTE, DENTIFRICE
Manufacturer: Haney, Inc.
Category: otc | Type: HUMAN OTC DRUG LABEL
Date: 20191007

ACTIVE INGREDIENTS: SODIUM FLUORIDE 1.5 mg/1 g
INACTIVE INGREDIENTS: CARBOXYPOLYMETHYLENE; POLYSORBATE 80; HYDRATED SILICA; TITANIUM DIOXIDE; CARBOXYMETHYLCELLULOSE SODIUM; COCONUT OIL; SORBITOL; SACCHARIN SODIUM; SODIUM LAURYL SULFATE; SODIUM HYDROXIDE; SODIUM ACID PYROPHOSPHATE; WATER; SUCRALOSE

Brisa Tropical Fresh

Drug Facts

Sodium fluoride 0.243%

(0.15% w/v fluoride ion)

Purpose

Anticavity toothpaste

Use

helps protect against cavities

Warning

Keep out of reach of children under 6 yrs. of age.

If more than used for brushing is accidentally swallowed, get medical help or contact a Poison Control Center right away.

Directions

- adults and children 2 yrs. & older: brush teeth thoroughly after meals or at least twice a day or use as directed by a dentist
- do not swallow
- to minimize swallowing use a pea-sized amount in children under 6
- supervise children's brushing until good habits are established
- children under 2 yrs.: ask a dentist

Inactive ingredients

water, sorbitol, hydrated silica, disodium pyrophosphate, sodium lauryl sulfate, flavor, cellulose gum, sodium hydroxide, sodium saccharin, carbomer, cocos nucifera (coconut) oil, sucralose, polysorbate 80, titanium dioxide

Questions?

1-888-654-6409

DISTR. BY/POR AGILE PURSUITS

CINCINNATI, OH 45202

116g tube in carton

brisa™

TOOTHPASTE

flouride toothpaste

Tropical Fresh

NET WT 4.1OZ (116g)